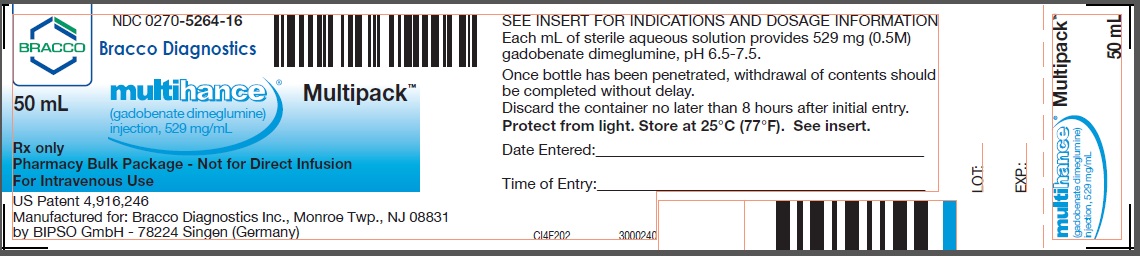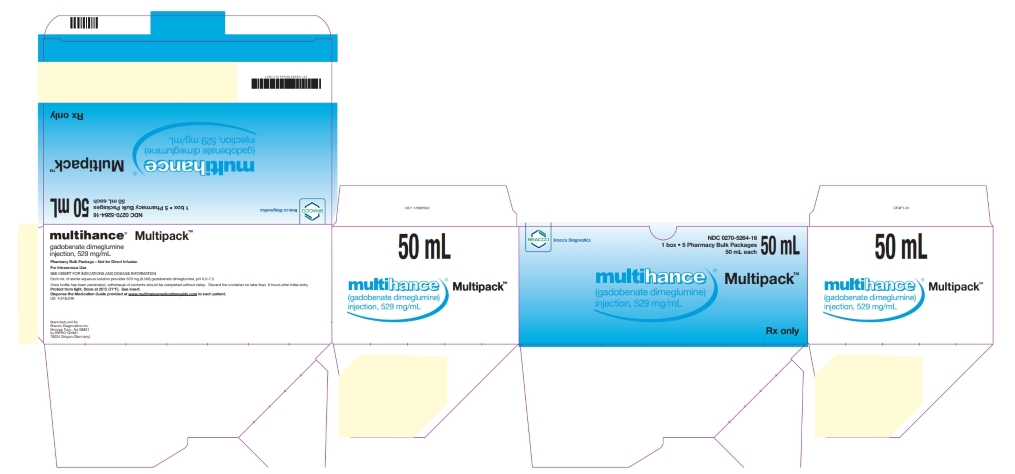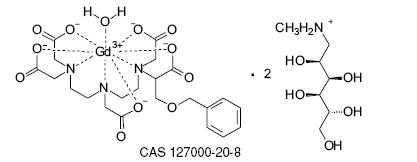 DRUG LABEL: MultiHance
NDC: 0270-5264 | Form: INJECTION, SOLUTION
Manufacturer: BRACCO DIAGNOSTICS INC
Category: prescription | Type: HUMAN PRESCRIPTION DRUG LABEL
Date: 20250316

ACTIVE INGREDIENTS: gadobenate dimeglumine 529 mg/1 mL

HIGHLIGHTS OF PRESCRIBING INFORMATION

These highlights do not include all the information needed to use MULTIHANCE safely and effectively. See full prescribing information for MULTIHANCE.
MultiHance (gadobenate dimeglumine) Injection
Initial U.S. Approval: 2004

WARNING: RISK ASSOCIATED WITH INTRATHECAL USE and NEPHROGENIC SYSTEMIC FIBROSIS

See full prescribing information for complete boxed warning

- Intrathecal administration of gadolinium based contrast agents (GBCAs) can cause serious adverse reactions including death, coma, encephalopathy, and seizures. MultiHance is not approved for intrathecal use. (5.1)
- GBCAs increase the risk for nephrogenic systemic fibrosis (NSF) among patients with impaired elimination of the drugs. Avoid use of MultiHance in these patients unless the diagnostic information is essential and not available with non-contrast MRI or other modalities. The risk for NSF appears highest among patients with:
  - chronic, severe kidney disease (GFR <30 mL/min/1.73m^2), or
  - acute kidney injury.
  Screen patients for acute kidney injury and other conditions that may reduce renal function. For patients at risk for chronically reduced renal function (e.g. age >60 years, hypertension or diabetes), estimate the glomerular filtration rate (GFR) through laboratory testing. (5.2)

1 INDICATIONS AND USAGE

- magnetic resonance imaging (MRI) of the central nervous system (CNS) in adults and pediatric patients (including term neonates), to visualize lesions with abnormal blood-brain barrier or abnormal vascularity of the brain, spine, and associated tissues (1.1)
- magnetic resonance angiography (MRA) to evaluate adults with known or suspected renal or aorto-ilio-femoral occlusive vascular disease. (1.2)

2 DOSAGE AND ADMINISTRATION

PHARMACY BULK PACKAGE – NOT FOR DIRECT INFUSION

- The recommended dose of MultiHance is 0.2 mL/kg (0.1 mmol/kg) administered as a rapid bolus intravenous injection.
- For MRI of the CNS in pediatric patients below 2 years of age the recommended dosage range is 0.1 to 0.2 mL/kg.
- To ensure complete injection of the contrast medium, follow the injection with a saline flush of at least 5 mL in MRI of the CNS and at least 20 mL in MRA. (2)

3 DOSAGE FORMS AND STRENGTHS

Each mL of MultiHance Injection contains 529 mg gadobenate dimeglumine. (3)

4 CONTRAINDICATIONS

MultiHance is contraindicated in patients with known allergic or hypersensitivity reactions to gadolinium-based contrast agents. (4)

5 WARNINGS AND PRECAUTIONS

- Hypersensitivity: anaphylactic/anaphylactoid reactions with cardiovascular, respiratory and cutaneous manifestations, ranging from mild to severe reactions including shock can occur. Monitor patients closely for need of emergency cardiorespiratory support. (5.3)
- Gadolinium is retained for months or years in brain, bone, and other organs. (5.4)

6 ADVERSE REACTIONS

The most commonly reported adverse reactions are nausea (1.3%) and headache (1.2%). (6)

To report SUSPECTED ADVERSE REACTIONS, contact Bracco Diagnostics Inc. at 1-800-257-5181 or FDA at 1-800-FDA-1088 or www.fda.gov/medwatch

8 USE IN SPECIFIC POPULATIONS

Pregnancy: Use only if imaging is essential during pregnancy and cannot be delayed. (8.1)

FULL PRESCRIBING INFORMATION

WARNING: RISK ASSOCIATED WITH INTRATHECAL USE and NEPHROGENIC SYSTEMIC FIBROSIS

Risk Associated with Intrathecal Use
Intrathecal administration of gadolinium-based contrast agents (GBCAs) can cause serious adverse reactions including death, coma, encephalopathy, and seizures. MultiHance is not approved for intrathecal use [see Warnings and Precautions (5.1)].

Nephrogenic Systemic Fibrosis
GBCAs increase the risk for nephrogenic systemic fibrosis (NSF) among patients with impaired elimination of the drugs. Avoid use of MultiHance in these patients unless the diagnostic information is essential and not available with non-contrasted MRI or other modalities. NSF may result in fatal or debilitating systemic fibrosis affecting the skin, muscle and internal organs.

The risk for NSF appears highest among patients with:

- chronic, severe kidney disease (GFR <30 mL/min/1.73m^2), or
- acute kidney injury.

Screen patients for acute kidney injury and other conditions that may reduce renal function. For patients at risk for chronically reduced renal function (e.g. age > 60 years, hypertension or diabetes), estimate the glomerular filtration rate (GFR) through laboratory testing.

For patients at highest risk for NSF, do not exceed the recommended MultiHance dose and allow a sufficient period of time for elimination of the drug from the body prior to re-administration. [see Warnings and Precautions (5.2)].

1 INDICATIONS AND USAGE

1.1 Magnetic Resonance Imaging (MRI) of the Central Nervous System (CNS)

MultiHance is indicated for intravenous use in magnetic resonance imaging (MRI) of the central nervous system (CNS) in adults and pediatric patients (including term neonates), to visualize lesions with abnormal blood-brain barrier or abnormal vascularity of the brain, spine, and associated tissues.

1.2 Magnetic Resonance Angiography (MRA) of Renal and Aorto-ilio-femoral Vessels

MultiHance is indicated for use in magnetic resonance angiography (MRA) to evaluate adults with known or suspected renal or aorto-ilio-femoral occlusive vascular disease.

2 DOSAGE AND ADMINISTRATION

2.1 Dosing and Imaging Instructions

2.1.1 MRI of the CNS

In adults and in pediatric patients over 2 years of age, the recommended dose of MultiHance for MRI of the CNS is 0.2 mL/kg (0.1 mmol/kg) administered as a rapid bolus intravenous injection. In pediatric patients below 2 years of age, the recommended dosage range is 0.1 to 0.2 mL/kg administered as a rapid bolus intravenous injection. To ensure complete injection of the contrast medium, follow the injection with a saline flush of at least 5 mL. Imaging of the CNS can be performed starting immediately after the bolus injection of MultiHance.

2.1.2 MRA of Renal and Aorto-ilio-femoral Vessels

For MRA examination, the recommended dose is 0.2 mL/kg (0.1 mmol/kg) administered as a rapid bolus intravenous injection followed by at least 20 mL saline flush either manually or using an automatic injector system. Start imaging immediately after the administration of MultiHance, with scan delay calculated by test bolus or automatic bolus detection technique. If an automatic contrast detection pulse sequence is not used for bolus timing, then a test bolus injection of 1-2 mL of MultiHance should be used to calculate the appropriate scan delay.

2.2 Dosing Table

TABLE 1: WEIGHT-BASED DOSING VOLUMES FOR:
CNS IMAGING (ADULTS AND PEDIATRICS ≥2 YEARS OF AGE*)
AND
MRA IMAGING (ADULTS ONLY)
 |  | 0.1mM/kg dose
Kilograms (Kg) | Pounds (lb) | Volume, Milliliters (mL)
2.5 | 5.5 | 0.5
5 | 11 | 1.0
10 | 22 | 2.0
15 | 33 | 3.0
20 | 44 | 4.0
25 | 55 | 5.0
30 | 66 | 6.0
35 | 77 | 7.0
40 | 88 | 8.0
45 | 99 | 9.0
50 | 110 | 10.0
55 | 121 | 11.0
60 | 132 | 12.0
65 | 143 | 13.0
70 | 154 | 14.0
75 | 165 | 15.0
80 | 176 | 16.0
85 | 187 | 17.0
90 | 198 | 18.0
95 | 209 | 19.0
100 | 220 | 20.0
105 | 231 | 21.0
110 | 242 | 22.0
115 | 253 | 23.0
120 | 264 | 24.0
125 | 275 | 25.0
130 | 286 | 26.0
135 | 297 | 27.0
140 | 308 | 28.0
145 | 319 | 29.0
150 | 330 | 30.0
*For pediatric patients less than 2 years of age, one-half of the per kg dose may be used.

2.3 Administration

Inspect the MultiHance vial visually for particulate matter and discoloration prior to administration. Do not use the solution if it is discolored or particulate matter is present. Draw MultiHance into a syringe and inject using sterile technique.

Do not mix intravenous medications or parenteral nutrition solutions with MultiHance. Do not administer other medications in the same intravenous line with MultiHance.

2.4 Directions for Proper Use of MultiHance Multipack

The pharmacy bulk package is used as a multiple dose container with an appropriate transfer device to fill empty syringes.

MultiHance Multipack injection should be drawn into the syringe and administered using sterile technique. Unused portions of the drug must be discarded.

When MultiHance Multipack injection is to be injected using plastic disposable syringes, the agent should be drawn into the syringe and used immediately.

1. The transferring of MultiHance (gadobenate dimeglumine) injection from the Pharmacy Bulk Package should be performed in a suitable work area, such as a laminar flow hood, utilizing aseptic technique.
2. The container closure may be penetrated only one time, utilizing a suitable transfer device. Once the pharmacy bulk package is punctured, it should not be removed from the aseptic work area during the entire period of use.
3. The withdrawal of container contents should be accomplished without delay. However, should this not be possible, a maximum time of 8 hours from initial closure entry is permitted to complete fluid transfer operation. Any unused MultiHance Multipack injection must be discarded 8 hours after initial puncture of the bulk package.
4. Temperature of container after the closure has been entered should not exceed 25°C (77°F).

3 DOSAGE FORMS AND STRENGTHS

MultiHance is a sterile, nonpyrogenic, clear, colorless to slightly yellow aqueous solution for intravenous use only, containing 529 mg gadobenate dimeglumine per mL.

4 CONTRAINDICATIONS

MultiHance is contraindicated in patients with known allergic or hypersensitivity reactions to gadolinium-based contrast agents [see Warnings and Precautions (5.3)].

5 WARNINGS AND PRECAUTIONS

5.1 Risk Associated with Intrathecal Use

Intrathecal administration of GBCAs can cause serious adverse reactions including death, coma, encephalopathy, and seizures. The safety and effectiveness of MultiHance have not been established with intrathecal use. MultiHance is not approved for intrathecal use [see Dosage and Administration (2.1)].

5.2 Nephrogenic Systemic Fibrosis

GBCAs increase the risk for nephrogenic systemic fibrosis (NSF) among patients with impaired elimination of the drugs. Avoid use of MultiHance among these patients unless the diagnostic information is essential and not available with non-contrast enhanced MRI or other modalities. The GBCA-associated NSF risk appears highest for patients with chronic, severe kidney disease (GFR <30 mL/min/1.73m^2) as well as patients with acute kidney injury. The risk appears lower for patients with chronic, moderate kidney disease (GFR 30-59 mL/min/1.73m^2) and little, if any, for patients with chronic, mild kidney disease (GFR 60-89 mL/min/1.73m^2). NSF may result in fatal or debilitating fibrosis affecting the skin, muscle and internal organs. Report any diagnosis of NSF following MultiHance administration to Bracco Diagnostics (1-800-257-5181) or FDA (1-800-FDA-1088 or www.fda.gov/medwatch).

Screen patients for acute kidney injury and other conditions that may reduce renal function. Features of acute kidney injury consist of rapid (over hours to days) and usually reversible decrease in kidney function, commonly in the setting of surgery, severe infection, injury or drug-induced kidney toxicity. Serum creatinine levels and estimated GFR may not reliably assess renal function in the setting of acute kidney injury. For patients at risk for chronically reduced renal function (e.g., age >60 years, diabetes mellitus or chronic hypertension), estimate the GFR through laboratory testing.

Among the factors that may increase the risk for NSF are repeated or higher than recommended doses of a GBCA and the degree of renal impairment at the time of exposure. Record the specific GBCA and the dose administered to a patient. For patients at highest risk for NSF, do not exceed the recommended MultiHance dose and allow a sufficient period of time for elimination of the drug prior to re-administration. For patients receiving hemodialysis, physicians may consider the prompt initiation of hemodialysis following the administration of a GBCA in order to enhance the contrast agent’s elimination. The usefulness of hemodialysis in the prevention of NSF is unknown [see Dosage and Administration (2) and Clinical Pharmacology (12)].

5.3 Hypersensitivity Reactions

Anaphylactic and anaphylactoid reactions have been reported, involving cardiovascular, respiratory, and/or cutaneous manifestations. Some patients experienced circulatory collapse and died. In most cases, initial symptoms occurred within minutes of MultiHance administration and resolved with prompt emergency treatment.

Prior to MultiHance administration, ensure the availability of personnel trained and medications to treat hypersensitivity reactions. If such a reaction occurs stop MultiHance and immediately begin appropriate therapy. Additionally, consider the risk for hypersensitivity reactions, especially in patients with a history of hypersensitivity reactions or a history of asthma or other allergic disorders. Observe patients for signs and symptoms of a hypersensitivity reaction during and for up to 2 hours after MultiHance administration.

5.4 Gadolinium Retention

Gadolinium is retained for months or years in several organs. The highest concentrations (nanomoles per gram of tissue) have been identified in the bone, followed by other organs (e.g. brain, skin, kidney, liver, and spleen). The duration of retention also varies by tissue and is longest in bone. Linear GBCAs cause more retention than macrocyclic GBCAs. At equivalent doses, gadolinium retention varies among the linear agents with Omniscan (gadodiamide) and Optimark (gadoversetamide) causing greater retention than other linear agents [Eovist (gadoxetate disodium), Magnevist (gadopentetate dimeglumine), MultiHance (gadobenate dimeglumine)]. Retention is lowest and similar among the macrocyclic GBCAs [Dotarem (gadoterate meglumine), Gadavist (gadobutrol), ProHance (gadoteridol)]. Consequences of gadolinium retention in the brain have not been established. Pathologic and clinical consequences of GBCA administration and retention in skin and other organs have been established in patients with impaired renal function [see Warnings and Precautions (5.2)]. There are rare reports of pathologic skin changes in patients with normal renal function. Adverse events involving multiple organ systems have been reported in patients with normal renal function without an established causal link to gadolinium retention [see Adverse Reactions (6.2)].

While clinical consequences of gadolinium retention have not been established in patients with normal renal function, certain patients might be at higher risk. These include patients requiring multiple lifetime doses, pregnant and pediatric patients, and patients with inflammatory conditions. Consider the retention characteristics of the agent when choosing a GBCA for these patients. Minimize repetitive GBCA imaging studies, particularly closely spaced studies when possible.

5.5 Acute Renal Failure

In patients with renal insufficiency, acute renal failure requiring dialysis or worsening renal function have occurred with the use of gadolinium-based contrast agents. The risk of renal failure may increase with increasing dose of the contrast agent. Screen all patients for renal dysfunction by obtaining a history and/or laboratory tests. Consider follow-up renal function assessments for patients with a history of renal dysfunction.

5.6 Extravasation and Injection Site Reactions

Extravasation of MultiHance may lead to injection site reactions, characterized by local pain or burning sensation, swelling, blistering, and necrosis. In animal experiments, local reactions including eschar and necrosis were noted even on Day 8 post perivenous injection of MultiHance. Exercise caution to avoid local extravasation during intravenous administration of MultiHance. If extravasation occurs, evaluate and treat as necessary if local reactions develop.

5.7 Cardiac Arrhythmias

Cardiac arrhythmias have been observed in patients receiving MultiHance in clinical trials [see Adverse Reactions (6.1)]. Assess patients for underlying conditions or medications that predispose to arrhythmias.

A double-blind, placebo-controlled, 24-hour post dose continuous monitoring, crossover study in 47 subjects evaluated the effect of 0.2 mmol/kg MultiHance on ECG intervals, including QTc. The average changes in QTc values compared with placebo were minimal (<5 msec). QTc prolongation between 30 and 60 msec were noted in 20 subjects who received MultiHance vs. 11 subjects who received placebo. Prolongations ≥61 msec were noted in 6 subjects who received MultiHance and in 3 subjects who received placebo. None of these subjects had associated malignant arrhythmias. The effects on QTc by MultiHance dose, other drugs, and medical conditions were not systematically studied.

5.8 Interference with Visualization of Certain Lesions

Certain lesions seen on non-contrast images may not be seen on contrast- images. Exercise caution when interpreting contrast MR images in the absence of companion non-contrast MR images.

6 ADVERSE REACTIONS

The following adverse reactions are discussed in greater detail in other sections of the label:

- Nephrogenic systemic fibrosis [see Warnings and Precautions (5.2)]
- Hypersensitivity reactions [see Warnings and Precautions (5.3)]

6.1 Clinical Trials Experience

Because clinical trials are conducted under widely varying conditions, adverse reaction rates observed in the clinical trials of a drug cannot be directly compared to rates in the clinical trials of another drug and may not reflect the rates observed in practice.

Adults

In clinical trials with MultiHance, a total of 4967 adult subjects (137 healthy volunteers and 4830 patients) received MultiHance at doses ranging from 0.005 to 0.4 mmol/kg. There were 2838 (57%) men and 2129 (43%) women with a mean age of 56.5 years (range 18 to 93 years). A total of 4403 (89%) subjects were Caucasian, 134 (3%) Black, 275 (6%) Asian, 40 (1%) Hispanic, 70 (1%) in other racial groups, and for 45 (1%) subjects, race was not reported.

The most commonly reported adverse reactions in adult subjects who received MultiHance were nausea (1.3%) and headache (1.2%). Most adverse reactions were mild to moderate in intensity. One subject experienced a serious anaphylactoid reaction with laryngeal spasm and dyspnea [see Warnings and Precautions (5.3)]. Serious adverse reactions consisting of convulsions, pulmonary edema, acute necrotizing pancreatitis, and anaphylactoid reactions were reported in 0.1% of subjects in clinical trials.

Adverse reactions that occurred in at least 0.5% of 4967 adult subjects who received MultiHance are listed below (Table 2), in decreasing order of occurrence within each system.

TABLE 2: ADVERSE REACTIONS REPORTED IN ≥ 0.5% OF ADULT SUBJECTS WHO RECEIVED MULTIHANCE IN CLINICAL TRIALS
Number of subjects dosed | 4967
Number of subjects with any adverse reaction | 517 (10.4%)
Gastrointestinal Disorders
Nausea | 67 (1.3%)
General Disorders and Administration Site Disorders
Injection Site Reaction | 54 (1.1%)
Feeling Hot | 49 (1.0%)
Nervous System Disorders
Headache | 60 (1.2%)
Dysgeusia | 33 (0.7%)
Paresthesia | 24 (0.5%)
Dizziness | 24 (0.5%)

The following adverse reactions occurred in less than 0.5% of the 4967 adult subjects who received MultiHance. Serious adverse reactions described above are not repeated below.
Blood and Lymphatic System Disorders: Basophilia;
Cardiac Disorders: Atrioventricular block first degree;
Eye Disorders: Eye pruritus, eye swelling, ocular hyperemia, visual disturbance;
Gastrointestinal Disorders: Abdominal pain or discomfort, diarrhea, dry mouth, lip swelling, paresthesia oral, tongue edema, vomiting;
General Disorders and Administration Site Conditions: Chest pain or discomfort, chills, malaise;
Immune System Disorders: Hypersensitivity;
Investigations: Nonspecific changes in laboratory tests (including hematology, blood chemistry, liver enzymes and urinalysis), blood pressure and electrocardiogram parameters (including PR, QRS and QT intervals and ST-T segment changes).
Musculoskeletal and Connective Tissue Disorders: Myalgia;
Nervous System Disorders: Parosmia, tremor;
Respiratory, Thoracic and Mediastinal Disorders: Dyspnea, laryngospasm, nasal congestion, sneezing, wheezing;
Skin and Subcutaneous Tissue Disorders: Hyperhidrosis, pruritus, rash, swelling face, urticaria.

Pediatric Patients
In clinical trials of MultiHance in MRI of the CNS, 307 pediatric subjects received MultiHance at a dose of 0.1 mmol/kg. A total of 160 (52%) subjects were male and the overall mean age was 6.0 years (range, 2 days to 17 years). A total of 211 (69%) subjects were Caucasian, 24 (8%) Black, 15 (5%) Asian, 39 (13%), Hispanic, 2 (<1%) in other racial groups, and for 16 (5%), race was not reported.

Adverse reactions were reported for 14 (4.6%) of the subjects. The frequency and the nature of the adverse reactions were similar to those seen in the adult patients. The most commonly reported adverse reactions were vomiting (1.0%), pyrexia (0.7%), and hyperhidrosis (0.7%). No subject died during study participation.

6.2 Postmarketing Experience

The following adverse reactions have been identified during post approval use of MultiHance or other GBCAs. Because these reactions are reported voluntarily from a population of uncertain size, it is not always possible to reliably estimate their frequency or establish a causal relationship to drug exposure.

Gastrointestinal Disorders: Acute pancreatitis with onset within 48 hours after GBCA administration.

Immune System Disorders: Anaphylactic, anaphylactoid and hypersensitivity reactions manifested with various degrees of severity up to anaphylactic shock, loss of consciousness and death. The reactions generally involved signs or symptoms of respiratory, cardiovascular, and/or mucocutaneous abnormalities.

General Disorders and Administration Site Conditions: Extravasation of MultiHance may lead to injection site reactions, characterized by local pain or burning sensation, swelling, blistering, and necrosis [see Warnings and Precautions (5.5)].

Adverse events with variable onset and duration have been reported after GBCA administration [see Warnings and Precautions (5.4)]. These include fatigue, asthenia, pain syndromes, and heterogeneous clusters of symptoms in the neurological, cutaneous, and musculoskeletal systems.

Respiratory, Thoracic and Mediastinal Disorders: Acute respiratory distress syndrome, pulmonary edema

Skin: Gadolinium associated plaques.

7 DRUG INTERACTIONS

7.1 Transporter-Based Drug-Drug Interactions

MultiHance and other drugs may compete for the canalicular multispecific organic anion transporter (MOAT also referred to as MRP2 or ABCC2). Therefore MultiHance may prolong the systemic exposure of drugs such as cisplatin, anthracyclines (e.g. doxorubicin, daunorubicin), vinca alkaloids (e.g. vincristine), methotrexate, etoposide, tamoxifen, and paclitaxel. In particular, consider the potential for prolonged drug exposure in patients with decreased MOAT activity (e.g. Dubin Johnson syndrome).

8 USE IN SPECIFIC POPULATIONS

8.1 Pregnancy

Risk Summary
GBCAs cross the placenta and result in fetal exposure and gadolinium retention. The human data on the association between GBCAs and adverse fetal outcomes are limited and inconclusive (see Data). In animal reproduction studies, gadobenate dimeglumine has been shown to be teratogenic in rabbits following repeated intravenous administration during organogenesis at doses up to 6 times the recommended human dose. There were no adverse developmental effects observed in rats with intravenous administration of gadobenate dimeglumine during organogenesis at doses up to three times the recommended human dose (see Data). Because of the potential risks of gadolinium to the fetus, use MultiHance only if imaging is essential and cannot be delayed.

The estimated background risk of major birth defects and miscarriage for the indicated population is unknown. All pregnancies have a background risk of birth defect, loss, or other adverse outcomes. In the U.S. general population, the estimated background risk of major birth defects and miscarriage in clinically recognized pregnancies is 2 to 4% and is 15 to 20%, respectively.

Data
Human Data
Contrast enhancement is visualized in the placenta and fetal tissues after maternal GBCA administration.

Cohort studies and case reports on exposure to GBCAs during pregnancy have not reported a clear association between GBCAs and adverse effects in the exposed neonates. However, a retrospective cohort study, comparing pregnant women who had a GBCA MRI to pregnant women who did not have an MRI, reported a higher occurrence of stillbirths and neonatal deaths in the group receiving GBCA MRI. Limitations of this study include a lack of comparison with non-contrast MRI and lack of information about the maternal indication for MRI. Overall, these data preclude a reliable evaluation of the potential risk of adverse fetal outcomes with the use of GBCAs in pregnancy.

Animal Data
Gadolinium Retention
GBCAs administered to pregnant non-human primates (0.1 mmol/kg on gestational days 85 and 135) result in measurable gadolinium concentration in the offspring in bone, brain, skin, liver, kidney, and spleen for at least 7 months. GBCAs administered to pregnant mice (2 mmol/kg daily on gestational days 16 through 19) result in measurable gadolinium concentrations in the pups in bone, brain, kidney, liver, blood, muscle, and spleen at one month postnatal age.

Reproductive Toxicology
Gadobenate dimeglumine has been shown to be teratogenic in rabbits when administered intravenously at 2 mmol/kg/day (6 times the recommended human dose based on body surface area) during organogenesis (day 6 to 18) inducing microphthalmia/small eye and/or focal retinal fold in 3 fetuses from 3 separate litters. In addition, MultiHance administered intravenously at 3 mmol/kg/day (10 times the recommended human dose based on body surface area) has been shown to increase intrauterine deaths in rabbits. There was no evidence that MultiHance induced teratogenic effects in rats at doses up to 2 mmol/kg/day (3 times the recommended human dose based on body surface area), however, rat dams exhibited no systemic toxicity at this dose. There were no adverse effects on the birth, survival, growth, development and fertility of the F1 generation at doses up to 2 mmol/kg in a rat peri- and post-natal (Segment III) study.

8.2 Lactation

Risk Summary
Limited literature reports that breastfeeding after gadobenate dimeglumine administration to the mother would result in the infant receiving an oral dose of 0.001%-0.04% of the maternal dose. There is no information on the effects of the drug on the breastfed infant or the effects of the drug on milk production. Additionally, there is limited GBCA gastrointestinal absorption. The developmental and health benefits of breastfeeding should be considered together with the mother’s clinical need for MultiHance and any potential adverse effects on the breastfed infant from MultiHance or from the underlying maternal condition.

8.4 Pediatric Use

MultiHance is approved for intravenous use for MRI of the CNS to visualize lesions with abnormal blood brain barrier or abnormal vascularity of the brain, spine, and associated tissues in pediatric patients from birth, including term neonates, to less than 17 years of age. Pediatric use is based on evidence of effectiveness in adults and in 202 pediatric patients 2 years of age and older, in addition to experience in 105 pediatric patients birth to less than 2 years of age that supported extrapolation from adult data [see Clinical Studies (14)]. Adverse reactions in pediatric patients were similar to those reported in adults [see Adverse Reactions (6.1)]. No dose adjustment according to age is necessary in pediatric patients two years of age and older. For pediatric patients, less than 2 years of age, the recommended dosage range is 0.1 to 0.2 mL/kg [see Dosage and Administration (2.1), Pharmacokinetics (12.3)]. The safety of MultiHance has not been established in preterm neonates.

8.5 Geriatric Use

Of the total number of 4967 adult subjects in clinical studies of MultiHance, 33% were 65 or older. No overall differences in safety or effectiveness were observed between these elderly subjects and the younger subjects.

The drug is known to be substantially excreted by the kidney, and the risk of toxic reactions to MultiHance may be greater in patients with impaired renal function. Because elderly patients are more likely to have decreased renal function it may be useful to monitor renal function.

10 OVERDOSAGE

Clinical consequences of overdosage with MultiHance have not been reported. Treatment of an overdosage should be directed toward support of vital functions and prompt institution of symptomatic therapy. In a Phase 1 clinical study, doses up to 0.4 mmol/kg were administered to patients. MultiHance has been shown to be dialyzable [see Clinical Pharmacology (12.3)].

11 DESCRIPTION

MultiHance injection is supplied as a sterile, nonpyrogenic, clear, colorless to slightly yellow aqueous solution intended for intravenous use only. Each mL of MultiHance contains 529 mg gadobenate dimeglumine and water for injection. MultiHance contains no preservatives.

Gadobenate dimeglumine is chemically designated as (4RS)-[4-carboxy-5,8,11-tris(carboxymethyl)- 1-phenyl-2-oxa-5,8,11-triazatridecan-13-oato(5-)] gadolinate(2-) dihydrogen compound with 1-deoxy-1-(methylamino)-D-glucitol (1:2) with a molecular weight of 1058.2 and an empirical formula of C22H28GdN3O11 • 2C7H17NO5. The structural formula is as follows:

MultiHance has a pH of 6.5-7.5. Pertinent physicochemical parameters are provided below:

Osmolality | 1.970 osmol/kg @ 37°C
Viscosity | 5.3 mPas @ 37°C
Density | 1.220 g/mL @ 20°C

MultiHance has an osmolality 6.9 times that of plasma (285 mOsmol/kg water) and is hypertonic under conditions of use.

12 CLINICAL PHARMACOLOGY

12.1 Mechanism of Action

Gadobenate dimeglumine is a paramagnetic agent and, as such, develops a magnetic moment when placed in a magnetic field. The large magnetic moment produced by the paramagnetic agent results in a large local magnetic field, which can enhance the relaxation rates of water protons in its vicinity leading to an increase of signal intensity (brightness) of tissue.

In magnetic resonance imaging (MRI), visualization of normal and pathological tissue depends in part on variations in the radiofrequency signal intensity that occur with 1) differences in proton density; 2) differences of the spin-lattice or longitudinal relaxation times (T1); and 3) differences in the spin-spin or transverse relaxation time (T2). When placed in a magnetic field, gadobenate dimeglumine decreases the T1 and T2 relaxation time in target tissues. At recommended doses, the effect is observed with greatest sensitivity in the T1-weighted sequences.

12.2 Pharmacodynamics

Unlike other tested paramagnetic contrast agents (See Table 3), MultiHance demonstrates weak and transient interactions with serum proteins that causes slowing in the molecular tumbling dynamics, resulting in strong increases in relaxivity in solutions containing serum proteins. The improved relaxation effect can contribute to increased contrast-to-noise ratio and lesion-to-brain ratio, which may improve visualization.

TABLE 3: RELAXIVITY (mM^–1s^–1) OF GADOLINIUM CHELATES
 | Human plasma
 | r1 | r2
Gadobenate | 9.7^1 | 12.5^1
Gadopentetate | 4.9^1 | 6.3^1
Gadodiamide | 5.4^2 | --
Gadoteridol | 5.4^2 | --
r1 and r2 relaxivities indicate the efficiency in shortening T1 and T2 relaxation times, respectively.
^1 In heparinized human plasma, at 39°C.
^2 In citrated human plasma, at 37°C.
-- Not available

Disruption of the blood-brain barrier or abnormal vascularity allows enhancement by MultiHance of lesions such as neoplasms, abscesses, and infarcts. Uptake of MultiHance into hepatocytes has been demonstrated.

12.3 Pharmacokinetics

Three single-dose intravenous studies were conducted in 32 healthy male subjects to assess the pharmacokinetics of gadobenate dimeglumine. The doses administered in these studies ranged from 0.005 to 0.4 mmol/kg. Upon injection, the meglumine salt is completely dissociated from the gadobenate dimeglumine complex. Thus, the pharmacokinetics is based on the assay of gadobenate ion, the MRI contrast effective ion in gadobenate dimeglumine. Data for plasma concentration and area under the curve demonstrated linear dependence on the administered dose. The pharmacokinetics of gadobenate ion following intravenous administration can be best described using a two-compartment model.

Distribution
Gadobenate ion has a rapid distribution half-life (reported as mean ± SD) of 0.084 ± 0.012 to 0.605 ± 0.072 hours. Volume of distribution of the central compartment ranged from 0.074 ± 0.017 to 0.158 ± 0.038 L/kg, and estimates of volume of distribution by area ranged from 0.170 ± 0.016 to 0.282 ± 0.079 L/kg. These latter estimates are approximately equivalent to the average volume of extracellular body water in man. In vitro studies showed no appreciable binding of gadobenate ion to human serum proteins. Following GBCA administration, gadolinium is present for months or years in brain, bone, skin, and other organs [see Warnings and Precautions (5.4)].

Elimination
Gadobenate ion is eliminated predominately via the kidneys, with 78% to 96% of an administered dose recovered in the urine. Total plasma clearance and renal clearance estimates of gadobenate ion were similar, ranging from 0.093 ± 0.010 to 0.133 ± 0.270 L/hr/kg and 0.082 ± 0.007 to 0.104 ± 0.039 L/hr/kg, respectively. The clearance is similar to that of substances that are subject to glomerular filtration. The mean elimination half-life ranged from 1.17 ± 0.26 to 2.02 ± 0.60 hours. A small percentage of the administered dose (0.6% to 4%) is eliminated via the biliary route and recovered in feces.

Metabolism
There was no detectable biotransformation of gadobenate ion. Dissociation of gadobenate ion in vivo has been shown to be minimal, with less than 1% of the free chelating agent being recovered alone in feces.

Pharmacokinetics in Special Population

Renal Impairment: A single intravenous dose of 0.2 mmol/kg of MultiHance was administered to 20 subjects with impaired renal function (6 men and 3 women with moderate renal impairment [urine creatinine clearance >30 to <60 mL/min] and 5 men and 6 women with severe renal impairment [urine creatinine clearance >10 to <30 mL/min]). Mean estimates of the elimination half-life were 6.1 ± 3.0 and 9.5 ± 3.1 hours for the moderate and severe renal impairment groups, respectively as compared with 1.0 to 2.0 hours in healthy volunteers.

Hemodialysis: A single intravenous dose of 0.2 mmol/kg of MultiHance was administered to 11 subjects (5 males and 6 females) with end-stage renal disease requiring hemodialysis to determine the pharmacokinetics and dialyzability of gadobenate. Approximately 72% of the dose was recovered by hemodialysis over a 4-hour period. The mean elimination half-life on dialysis was 1.21 ± 0.29 hours as compared with 42.4 ± 24.4 hours when off dialysis.

Hepatic Impairment: A single intravenous dose of 0.1 mmol/kg of MultiHance was administered to 11 subjects (8 males and 3 females) with impaired liver function (Class B or C modified Child-Pugh Classification). Hepatic impairment had little effect on the pharmacokinetics of MultiHance with the parameters being similar to those calculated for healthy subjects.

Gender, Age, Race: A multiple regression analysis performed using pooled data from several pharmacokinetic studies found no significant effect of sex upon the pharmacokinetics of gadobenate. Clearance appeared to decrease slightly with increasing age. Since variations due to age appeared marginal, dosage adjustment for geriatric population is not recommended. Pharmacokinetic differences due to race have not been systematically studied.

Pediatric: A population pharmacokinetic analysis incorporated data from 25 healthy subjects (14 males and 11 females) and 15 subjects undergoing MR imaging of the central nervous system (7 males and 8 females) between ages of 2 and 16 years. The subjects received a single intravenous dose of 0.1 mmol/kg of MultiHance. The geometric mean Cmax was 62.3 μg/mL (n=16) in children 2 to 5 years of age, and 64.2 μg/mL (n=24) in children older than 5 years. The geometric mean AUC 0-∞ was 77.9 μg⋅h/mL in children 2-5 years of age (n=16) and 82.6 μg⋅h/mL in children older than 5 years (n=24). The geometric mean half-life was 1.2 hours in children 2 to 5 years of age and 0.93 hours in children older than 5 years. There was no significant gender-related difference in the pharmacokinetic parameters in the pediatric patients. Over 80% of the dose was recovered in urine after 24 hours. Pharmacokinetic simulations indicate similar AUC and Cmax values for MultiHance in pediatric subjects less than 2 years when compared to those reported for adults; no age-based dose adjustment is necessary for this pediatric population.

13 NONCLINICAL TOXICOLOGY

13.1 Carcinogenesis, Mutagenesis, Impairment of Fertility

Long-term animal studies have not been performed to evaluate the carcinogenic potential of MultiHance.

The results for MultiHance were negative in the following genetic toxicity studies: 1) in vitro bacteria reverse mutation assays, 2) an in vitro gene mutation assay in mammalian cells, 3) an in vitro chromosomal aberration assay, 4) an in vitro unscheduled DNA synthesis assay, and 5) an in vivo micronucleus assay in rats.

MultiHance had no effect on fertility and reproductive performance at IV doses of up to 2 mmol/kg/day (3 times the human dose on body surface basis) for 13 weeks in male rats and for 32 days in female rats. However, vacuolation in testes and abnormal spermatogenic cells were observed when MultiHance was intravenously administered to male rats at 3 mmol/kg/day (5 times the human dose on body surface basis) for 28 days. The effects were not reversible following 28-day recovery period. The effects were not reported in dog and monkey studies (at doses up to about 11 and 10 times the human dose on body surface basis for dogs (28 days dosing) and monkeys (14 days dosing), respectively).

14 CLINICAL STUDIES

14.1 MRI of the CNS

Adults:
MultiHance was evaluated in 426 adult patients in 2 controlled clinical trials of the central nervous system (Study A and Study B), enrolling 217 men and 209 women with a mean age of 52 years (range 18 to 88 years). The racial and ethnic representations were 88% Caucasian, 6% Black, 4% Hispanic, 1% Asian, and 1% other racial or ethnic groups. These trials were designed to compare MultiHance contrast MRI to non-contrast MRI alone. In Study A, patients highly suspected of having a lesion(s) of the CNS based on nuclear medicine imaging, computed tomography (CT), contrast CT, MRI, contrast- MRI, or angiography were randomized to receive two MRI evaluations with 0.05 mmol/kg (n=140) or 0.1 mmol/kg (n=136) of MultiHance. In Study B, patients with known metastatic disease to the CNS were randomized to receive two MRI evaluations with 0.05 mmol/kg (n=74) or 0.1 mmol/kg (n=76) of MultiHance. MRI scans were performed pre-contrast and within 5 minutes after each injection. The studies were designed to evaluate the effect of MultiHance MRI compared to the non-contrast MRI on a lesion level. Pre-contrast, post-contrast, and pre-plus-post contrast images (paired images) were independently evaluated by three blinded readers. The images were evaluated for the following endpoints using a scale from 0 to 4: the degree of lesion border delineation, the degree of visualization of lesion internal morphology, and the degree of lesion contrast enhancement. Lesion counting was also performed for the pre-contrast and paired image sets.

The 0.1 mmol/kg dose of MultiHance demonstrated consistently better visualization for all readers for all visualization endpoints. However, the 0.05 mmol/kg dose of MultiHance provided inconsistent visualization results between readers.

Comparison of pre-contrast versus post-contrast (0.1 mmol/kg) images showed that the mean score differences were significant and favored contrast for subjects in Study B (all subjects with known metastatic lesions) and for subjects with known tumors in Study A. However, the mean score differences between the pre-contrast and post-contrast images were not significant for non-tumor patients in Study A. These negative results may be attributed to a lack of lesion enhancement in non-tumor CNS disease.

Table 4 shows a comparison of paired images (pre-and post-contrast) versus pre-contrast images with respect to the difference in the mean score and with respect to the proportion of lesions read as better, worse, or the same as the pre-contrast MRI images. Table 4 shows that based on a lesion-level analysis 0.1 mmol/kg MultiHance provided a statistically significant improvement for the three structural parameters evaluated. Also, more lesions were seen in the paired images than in the pre-contrast images alone.

Table 4: LESION LEVEL RESULTS OF MRI CENTRAL NERVOUS SYSTEM ADULT STUDIES WITH 0.1 mmol/kg MULTIHANCE
 | Study A |  |  | Study B
 | Reader 1 | Reader 2 | Reader 3 | Reader 1 | Reader 2 | Reader 3
Endpoints | N = 395 | N = 384 | N = 299 | N = 245 | N = 275 | N = 254
Border Delineation:
Difference of Means (a) | 0.8* | 0.6* | 0.8* | 1.8* | 1.5* | 1.9*
Worse (b) Same Better | 44 (11%) 146 (37%) 205 (52%) | 61 (16%) 168 (44%) 155 (40%) | 57 (19%) 89 (30%) 153 (51%) | 13 (5%) 11 (5%) 221 (90%) | 24 (9%) 19 (7%) 232 (84%) | 15 (6%) 18 (7%) 221 (87%)
Internal Morphology:
Difference of Means | 0.8* | 0.6* | 0.7* | 1.7* | 1.4* | 2.1*
Worse Same Better | 37 (10%) 147 (37%) 211 (53%) | 63 (17%) 151 (39%) 170 (44%) | 62 (21%) 84 (28%) 153 (51%) | 13 (5%) 16 (7%) 216 (88%) | 26 (10%) 22 (8%) 227 (82%) | 14 (5%) 22 (9%) 218 (86%)
Contrast Enhancement:
Difference of Means | 0.7* | 0.5* | 0.8* | 1.9* | 1.3* | 1.9*
Worse Same Better | 75 (19%) 148 (37%) 172 (44%) | 74 (19%) 152 (40%) 158 (41%) | 50 (17%) 109 (36%) 140 (47%) | 13 (5%) 11 (5%) 221 (90%) | 32 (12%) 21 (7%) 222 (81%) | 17 (7%) 14 (5%) 223 (88%)
(a) Difference of means = (paired mean) - (pre mean)
(b) Worse = paired score is less than the pre score
Same = paired score is the same as the pre score
Better = paired score is greater than the pre score
* Statistically significant for the mean (paired t test)

Pediatric 2 to 17 years
The efficacy and safety of MultiHance were evaluated in 92 pediatric patients with known or highly suspected disease of the central nervous system. MRI scans were performed pre-contrast and within 3 to 10 minutes following the administration of MultiHance 0.1 mmol/kg. Pre-contrast, post-contrast, and pre-plus-post contrast images (paired images) were independently evaluated by three blinded readers on a lesion level. The images were evaluated for the same endpoints as in the adult central nervous system trials using a scale from 0 to 4: the degree of lesion border delineation, the degree of visualization of lesion internal morphology, and the degree of lesion contrast enhancement. Lesion counting was also performed for the pre-contrast and paired image sets. The pre-contrast versus the paired image set was the primary comparison. Forty-nine percent of study subjects were male and the overall mean age was 10.6 years (range 2 to 17 years). The racial and ethnic representations were 77% Caucasian, 13% Asian, 5% Black, and 4% other racial or ethnic groups. MultiHance increased lesion border delineation, lesion internal morphology, and lesion contrast enhancement relative to non-contrast and these results were comparable to those seen in adults.

Pediatrics below 2 years
A study of 90 pediatric patients younger than 2 years of age was performed which supports extrapolation of CNS efficacy findings from adults and older pediatric patients. Three independent, blinded readers evaluated pre-contrast MRI image sets and paired pre-plus-post-contrast MRI image sets using MultiHance and rated the images according to three co-primary endpoints at a lesion level for the primary analysis. Two of the three readers reported improvement in the paired image sets in each of the three co-primary endpoints of lesion border delineation, visualization of lesion internal morphology, and lesion contrast enhancement.

14.2 MRA of Renal and Aorto-ilio-femoral Vessels

Safety and efficacy of MultiHance for use in MRA were evaluated in two prospective, multi-center, open-label, clinical trials (one for each arterial vascular territory: renal and aorto-ilio-femoral). Out of 580 patients who received Multihance in these two trials, 62.2% were men and 90.9% were Caucasian; the average age was 63.4 years (range 18 to 93 years). In both trials, patients with known or suspected arterial disease underwent MRA with and without MultiHance as well as catheter-based digital subtraction angiography (DSA). Assessment of diagnostic efficacy for detecting/excluding clinically significant steno-occlusive disease (≥ 51% stenosis measured with electronic calipers) was based on comparisons of sensitivity and specificity between MultiHance MRA and non-contrast MRA, with DSA as a reference standard.

In each vascular territory, the primary efficacy analyses were designed to demonstrate superiority in sensitivity and non-inferiority in specificity of MultiHance MRA to non-contrast MRA at the vessel-segment level. The interpretation of MRA images from both trials was conducted by three independent radiologist readers who were blinded to clinical data, including the DSA results. The pre-specified success criteria were to be achieved by at least the same two readers for all primary analyses.

Results of both trials showed a statistically significant increase in sensitivity and specificity of MultiHance MRA over non-contrast MRA in detecting clinically significant steno-occlusive disease.

Table 5 summarizes the efficacy results by reader.

TABLE 5. PERFORMANCE CHARACTERISTICS OF MULTIHANCE-MRA AND NON-CONTRAST MRA
READER | SENSITIVITY |  |  | SPECIFICITY
READER | AORTO-ILIO-FEMERAL ARTERIES
READER | MultiHance MRA [A] | Non-contrast MRA [B] | [A] – [B] (95% CI)* | MultiHance MRA [A] | Non-contrast MRA [B] | [A] – [B] (95% CI)*
1 | 77.8% | 73.7% | 4.5 (1.5, 7.6) | 88.1% | 78.5% | 10.0 (7.3, 12.6)
2 | 65.2% | 52.5% | 12.6 (8.5, 16.6) | 94.2% | 89.4% | 4.9 (2.7, 7.1)
3 | 69.0% | 59.1% | 10.0 (6.1, 14.0) | 90.0% | 75.3% | 14.9 (12.1, 17.8)
 | RENAL ARTERIES
 | SENSITIVITY |  |  | SPECIFICITY
 | MultiHance MRA [A] | Non-contrast MRA [B] | [A] – [B] (95% CI)* | MultiHance MRA [A] | Non-contrast MRA [B] | [A] – [B] (95% CI)*
1 | 67.8% | 47.0% | 20.8 (12.8, 28.9) | 94.0% | 86.1% | 8.3 (4.2, 12.4)
2 | 62.4% | 46.7% | 16.2 (6.8, 25.6) | 94.0% | 83.5% | 10.3 (5.5, 15.0)
3 | 65.5% | 39.6% | 25.3 (15.9, 34.6) | 94.7% | 87.3% | 8.0 (3.6, 12.5)

16 HOW SUPPLIED/STORAGE AND HANDLING

16.1 How Supplied
MultiHance Multipack (gadobenate dimeglumine) injection is a clear, colorless to slightly yellow solution containing 529 mg gadobenate dimeglumine per mL. MultiHance Multipack is supplied in glass bottles; each multidose bottle is rubber stoppered with an aluminum seal and the contents are sterile. MultiHance is supplied in boxes of:

Five 50 mL Pharmacy Bulk Packages (NDC 0270-5264-16)
Five 100 mL Pharmacy Bulk Packages (NDC 0270-5264-17)

16.2 Storage and Handling
Store at 25°C (77°F), excursions permitted to 15-30°C (59-86°F) [see USP Controlled Room Temperature]. Do not freeze.

17 PATIENT COUNSELING INFORMATION

- Advise the patient to read the FDA-approved patient labeling (Medication Guide) found at www.multihancemedicationguide.com.

Nephrogenic Systemic Fibrosis

Instruct patients to inform their physician if they:

- have a history of kidney and/or liver disease, or
- have recently received a GBCA.

GBCAs increase the risk for NSF among patients with impaired elimination of the drugs. To counsel patients at risk for NSF:

- Describe the clinical manifestations of NSF
- Describe procedures to screen for the detection of renal impairment.

Instruct the patients to contact their physician if they develop signs or symptoms of NSF following MultiHance administration, such as burning, itching, swelling, scaling, hardening and tightening of the skin; red or dark patches on the skin; stiffness in joints with trouble moving, bending or straightening the arms, hands, legs or feet; pain in the hip bones or ribs; or muscle weakness.

Common Adverse Reactions

Inform patients that they may experience:

- reactions along the venous injection site, such as mild and transient burning or pain or feeling of warmth or coldness at the injection site
- side effects of feeling hot, nausea, and headache.

Gadolinium Retention
Advise patients that gadolinium is retained for months or years in brain, bone, skin, and other organs in patients with normal renal function. The clinical consequences of retention are unknown. Retention depends on multiple factors and is greater following administration of linear GBCAs than following administration of macrocyclic GBCAs [see Warnings and Precautions (5.4)].

Rx only
US Patent No. 4,916,246

Manufactured for
Bracco Diagnostics Inc.
Princeton, NJ 08540

By BIPSO GmbH
78224 Singen (Germany)

Revised March 2025
CL4F7-09

MEDICATION GUIDE
MULTIHANCE (məl-tē-han(t)s)
(gadobenate dimeglumine)
Injection, for intravenous use

What is the most important information I should know about MULTIHANCE?

- GBCAs like MULTIHANCE may cause serious side effects including death, coma, encephalopathy, and seizures when it is given intrathecally (injection given into the spinal cord). It is not known if MULTIHANCE is safe and effective with intrathecal use. MULTIHANCE is not approved for this use.
- MULTIHANCE contains a metal called gadolinium. Small amounts of gadolinium can stay in your body including the brain, bones, skin and other parts of your body for a long time (several months to years).
- It is not known how gadolinium may affect you, but so far, studies have not found harmful effects in patients with normal kidneys.
- Rarely, patients have reported pains, tiredness, and skin, muscle or bone ailments for a long time, but these symptoms have not been directly linked to gadolinium.
- There are different GBCAs that can be used for your MRI exam. The amount of gadolinium that stays in the body is different for different gadolinium medicines. Gadolinium stays in the body more after Omniscan or Optimark than after Eovist, Magnevist, or MultiHance. Gadolinium stays in the body the least after Dotarem, Gadavist, or ProHance.
- People who get many doses of gadolinium medicines, women who are pregnant and young children may be at increased risk from gadolinium staying in the body.
- Some people with kidney problems who get gadolinium medicines can develop a condition with severe thickening of the skin, muscles and other organs in the body (nephrogenic systemic fibrosis). Your healthcare provider should screen you to see how well your kidneys are working before you receive MULTIHANCE.

What is MULTIHANCE?

- MULTIHANCE is a prescription medicine called a gadolinium-based contrast agent (GBCA). MULTIHANCE, like other GBCAs, is injected into your vein and used with a magnetic resonance imaging (MRI) scanner.
- An MRI exam with a GBCA, including MULTIHANCE, helps your doctor to see problems better than an MRI exam without a GBCA.
- Your doctor has reviewed your medical records and has determined that you would benefit from using a GBCA with your MRI exam.

Do not receive MULTIHANCE if you have had a severe allergic reaction to GBCAs including gadobenate dimeglumine, or any of the ingredients in MULTIHANCE.

Before receiving MULTIHANCE, tell your healthcare provider about all your medical conditions, including if you:

- have had any MRI procedures in the past where you received a GBCA. Your healthcare provider may ask you for more information including the dates of these MRI procedures.
- are pregnant or plan to become pregnant. It is not known if MULTIHANCE can harm your unborn baby. Talk to your healthcare provider about the possible risks to an unborn baby if a GBCA such as MULTIHANCE is received during pregnancy
- have kidney problems, diabetes, or high blood pressure.
- have had an allergic reaction to dyes (contrast agents) including GBCAs

What are the possible side effects of MULTIHANCE?

- See “What is the most important information I should know about MULTIHANCE?”
- Allergic reactions. MULTIHANCE can cause allergic reactions that can sometimes be serious. Your healthcare provider will monitor you closely for symptoms of an allergic reaction.

The most common side effects of MULTIHANCE include: nausea, headache, feeling hot, or burning at the injection site.
These are not all the possible side effects of MULTIHANCE.
Call your doctor for medical advice about side effects. You may report side effects to FDA at 1-800-FDA-1088.

General information about the safe and effective use of MULTIHANCE.
Medicines are sometimes prescribed for purposes other than those listed in a Medication Guide. You can ask your healthcare provider for information about MULTIHANCE that is written for health professionals.

What are the ingredients in MULTIHANCE?
Active ingredient: gadobenate dimeglumine
Inactive ingredients: water
Manufactured by: BIPSO GmbH-78224 Singen (Germany)
Manufactured for: Bracco Diagnostics Inc., Princeton, NJ 08540
US Patent No. 4,916,246
For more information, go to www.imaging.bracco.com or call 1-800-257-5181.

This Medication Guide has been approved by the U.S. Food and Drug Administration

Revised: 03/2025

PACKAGE LABEL

Multihance Multipack 50 mL
NDC 0270-5264-16